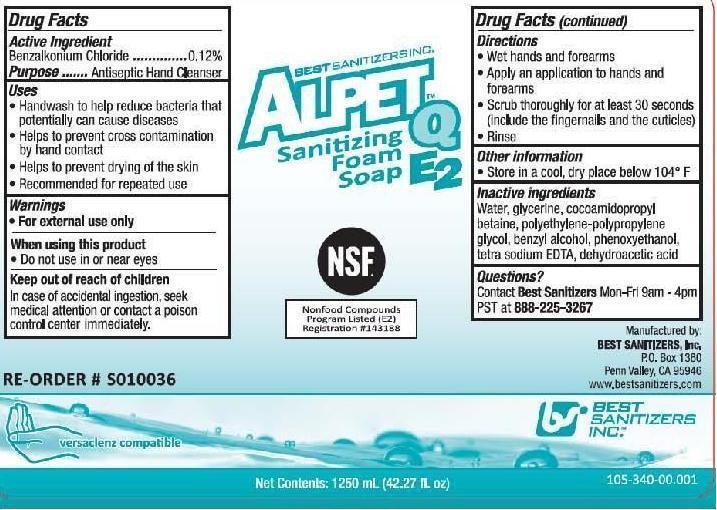 DRUG LABEL: Alpet Q E2
NDC: 59900-130 | Form: LIQUID
Manufacturer: Best Sanitizers, Inc
Category: otc | Type: HUMAN OTC DRUG LABEL
Date: 20241205

ACTIVE INGREDIENTS: BENZALKONIUM CHLORIDE 1.2 g/1000 mL
INACTIVE INGREDIENTS: WATER; GLYCERIN; COCAMIDOPROPYL BETAINE; POLYETHYLENE GLYCOL, UNSPECIFIED; BENZYL ALCOHOL; PHENOXYETHANOL; EDETIC ACID; DEHYDROACETIC ACID

ALPET Q E2 Sanitizing Foam Soap 5900-130

Active Ingredient

Benzalkonium Chloride 0.12%

Purpose

Antiseptic Hand Cleanser

Uses

- Hanwash to help reduce bacteria that potentially can cause diseases
- Helps to prevent cross contamination by hand contact
- Helps to prevent drying of the skin
- Recommended for repeated use

Warnings

- For external use only

When Using this product

- Do not use in or near eyes

Keep out of reach of children

In case of accidental ingestion, seek medical attention or contact a poison control center immediately.

Directions

- Wet hands and forearms
- Apply an application to hands and forearms
- Scrub thoroughly for at least 30 seconds (include the fingernails and the cuticles)
- Rinse

Other information

Store in a cool dry place below 104° F

Inactive ingredients

water, glycerine, cocoamidopropy betaine, polyethylene-polypropylene glycol, benzyl alcohol, phenoxyethanol, tetra sodium EDTA, dehydroacetic acid

Questions?

Contact Best SanitizersMon-Fri 9am-4pm PST at 888-225-3267

PACKAGE LABEL

Alpet Q E2 Sanitizing Foam Soap

NSF